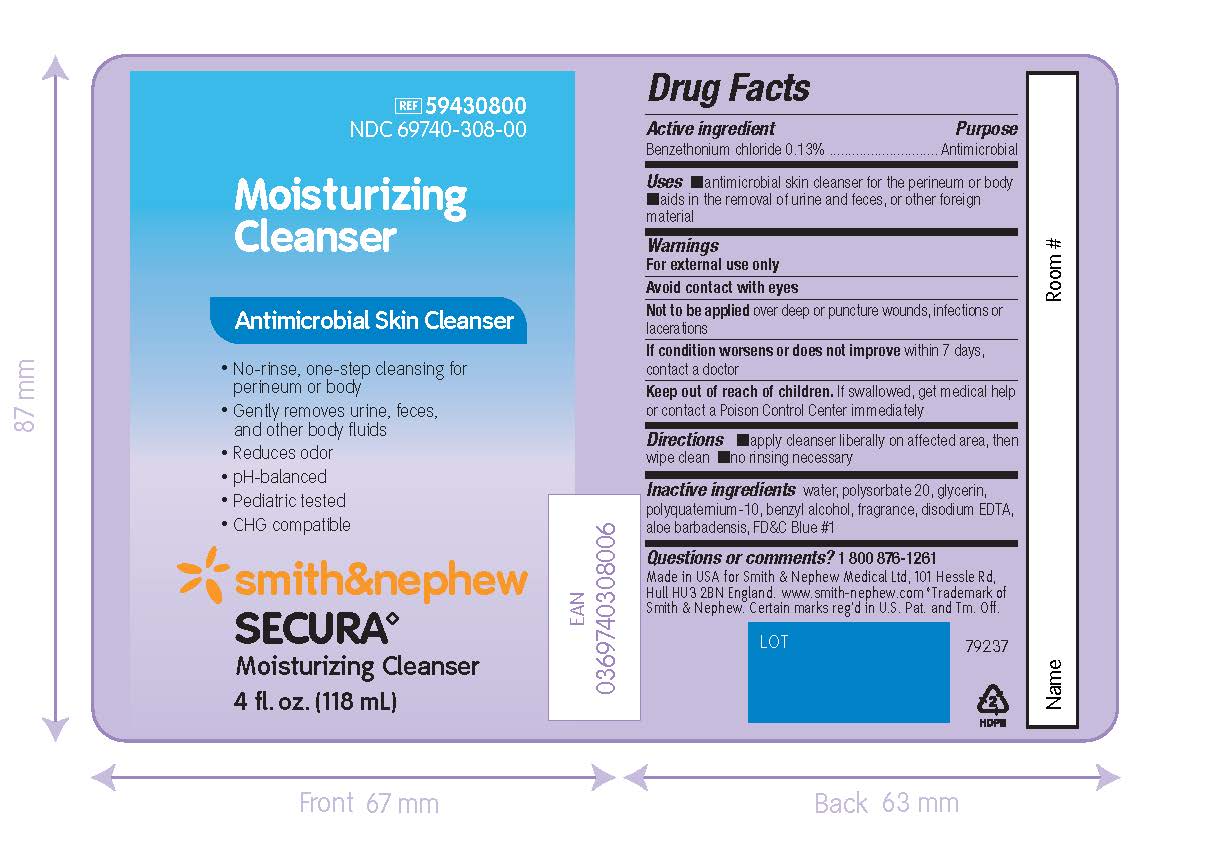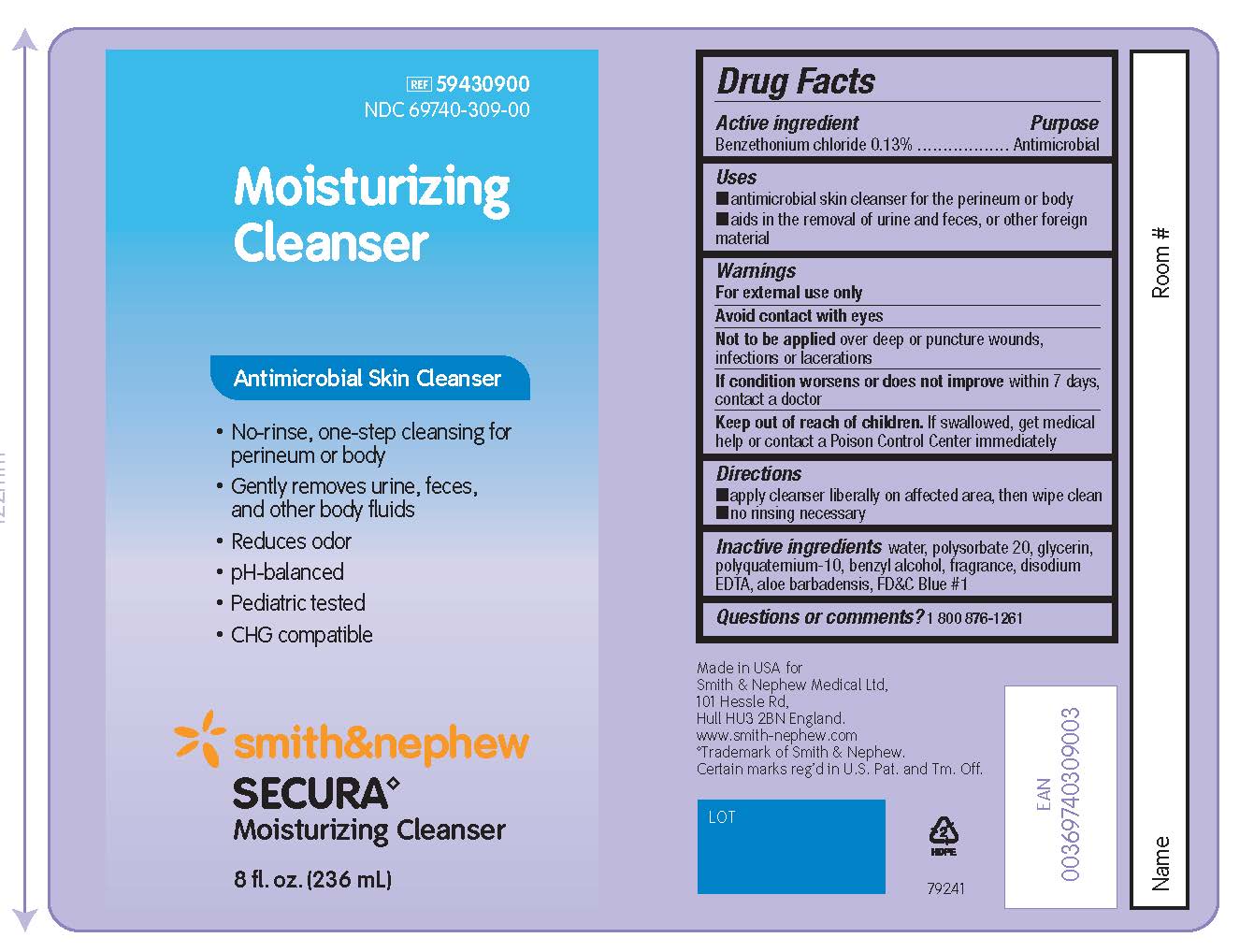 DRUG LABEL: Secura Moisturizing Cleanser
NDC: 69740-309 | Form: SPRAY
Manufacturer: Smith & Nephew Medical Ltd
Category: otc | Type: HUMAN OTC DRUG LABEL
Date: 20240816

ACTIVE INGREDIENTS: BENZETHONIUM CHLORIDE 1.3 ug/1 mL
INACTIVE INGREDIENTS: POLYQUATERNIUM-10 (125 MPA.S AT 2%); BENZYL ALCOHOL; FD&C BLUE NO. 1; ALOE VERA LEAF; GLYCERIN; POLYSORBATE 20; WATER; EDETATE DISODIUM

Secura Moisturizing Cleanser

ACTIVE INGREDIENT

Benzethonium chloride 0.13%

PURPOSE

Antimicrobial

USES

- antimicrobial skin cleanser for the perineum or body
- aids in the removal of urine and feces, or other foreign material

WARNINGS

WHEN USING

- For external use only
- Avoid contact with eyes

DO NOT USE

- Not to be appliedover deep or puncture wounds, infections or lacerations

STOP USE

- If condition worsens or does not improvewithin 7 days, contact a doctor

- Keep out of reach of children.If swallowed, get medical help or contact a Poison Control Center immediately

DIRECTIONS

- apply cleanser liberally on affected area, then wipe clean
- no rinsing necessary

INACTIVE INGREDIENTS

water, polysorbate 20, glycerin, polyquaternium-10, benzyl alcohol, fragrance, disodium EDTA, aloe barbadensis, FD&C Blue #1

QUESTION OR COMMENTS?

1 800 876-1261

PACKAGE LABEL - PRINCIPAL DISPLAY PANEL - SECURA MOISTURIZING CLEANSER (118mL)

REF 59430800

NDC69740-308-00

Moisturizing
Cleanser

Antimicrobial Skin Cleanser

- No-rinse, one-step cleansing for perineum or body
- Gently removes urine, feces, and other body fluids
- Reduces odor
- pH-balanced
- Pediatric-tested
- CHG compatible

Smith&Nephew
Secura◊
Moisturizing Cleanser

4 fl. oz. (118 mL)

Made in the USA for
Smith & Nephew Medical Ltd,
101 Hessle Road
Hull, HU3 2BN, England
www.smith-nephew.com
◊Trademark of Smith & Nephew.

Certain marks reg’d in US Patent Office and Tm. Off.

PACKAGE LABEL - PRINCIPAL DISPLAY PANEL - SECURA MOISTURIZING CLEANSER (236mL)

REF 59430900

NDC69740-309-00

Moisturizing
Cleanser

Antimicrobial Skin Cleanser

- No-rinse, one-step cleansing for perineum or body
- Gently removes urine, feces, and other body fluids
- Reduces odor
- pH-balanced
- Pediatric-tested
- CHG compatible

Smith&Nephew
Secura◊
Moisturizing Cleanser

8 fl. oz. (236 mL)

Made in the USA for
Smith & Nephew Medical Ltd,
101 Hessle Road
Hull, HU3 2BN, England
www.smith-nephew.com
◊Trademark of Smith & Nephew.

Certain marks reg’d in US Patent Office and Tm. Off.